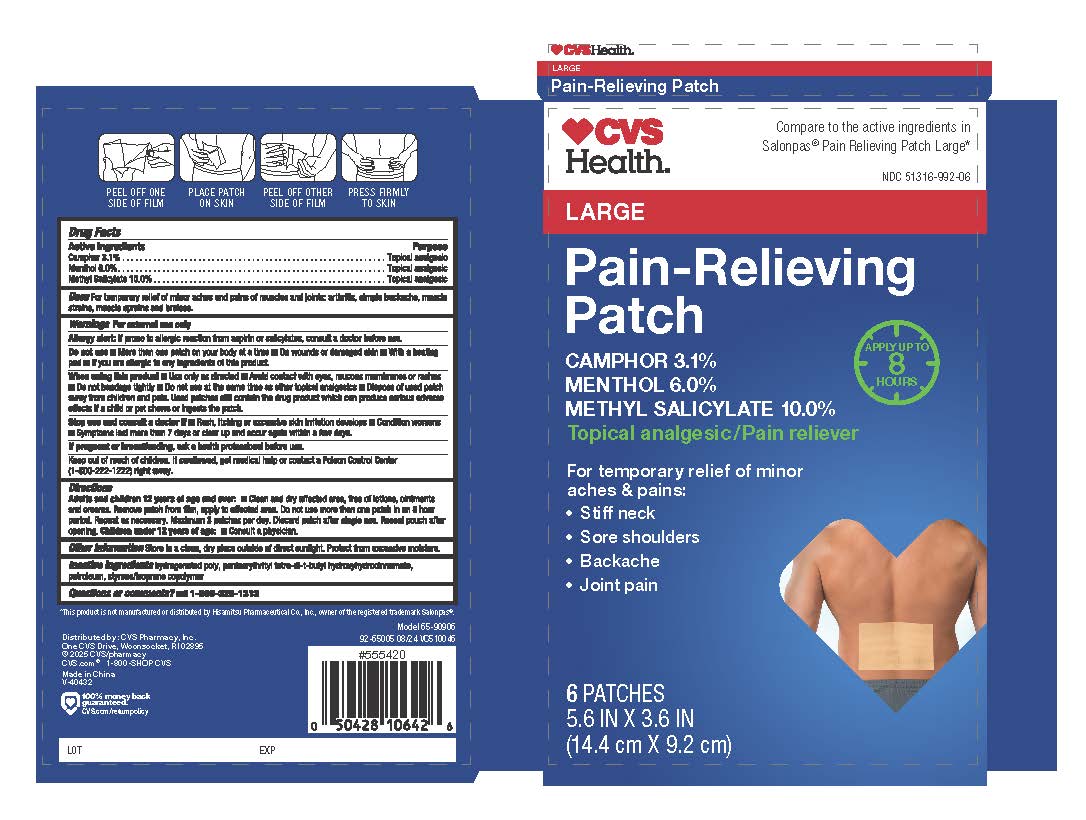 DRUG LABEL: CVS Health Pain-Relieving Patch
NDC: 51316-992 | Form: PATCH
Manufacturer: CVS Pharmacy, Inc.
Category: otc | Type: HUMAN OTC DRUG LABEL
Date: 20251228

ACTIVE INGREDIENTS: METHYL SALICYLATE 10 g/100 g; CAMPHOR (SYNTHETIC) 3.1 g/100 g; MENTHOL 6 g/100 g
INACTIVE INGREDIENTS: HYDROGENATED POLYDECENE TYPE I; STYRENE/ACRYLAMIDE COPOLYMER (MW 500000); PENTAERYTHRITOL TETRAKIS(3-(3,5-DI-TERT-BUTYL-4-HYDROXYPHENYL)PROPIONATE); LIQUID PETROLEUM

CVS Health Pain-Relieving Patch

Active Ingredients

Camphor 3.1%
Menthol 6.0%
Methyl Salicylate 10.0%

Purpose

Topical analgesic

Uses

For temporary relief of minor aches and pains of muscles and joints: arthritis, simple backache, muscle strains, muscle sprains, and bruises.

Warnings

For external use only

Allergy alert: If prone to allergic reaction from aspirin or salicylates, consult a doctor before
use.

Do not use■More than one patch on your body at a time■ On wounds or damaged skin■ With a heating
pad ■If you are allergic to any 1ngred1ents of this product

When using this product

■Use only as directed■ Avoid contact with eyes, mucous membranes or rashes ■ Do not bandage tightly ■ Do not use at the same time as other topical analgesics ■ Dispose of used patch away from children and pets. Used patches still contain the drug product which can produce serious adverse effects if a child or pet chews or ingests the patch.

Stop use and consult a doctor if

■Rash, itching or excessive skin irritation develops

■ Condition worsens
■Symptoms last more than 7 days or clear up and occur again within a few days.

If pregnant or breastfeeding

ask a health professional before use

Keep out of reach of children

If swallowed, get medical help or contact a Poison Control Center
(1-800-222-1222) right away

Directions

Adults and children 12 years of age and over: ■ Clean and dry affected area, free of lotions, ointments and creams. Remove patch from film, apply to affected area. Do not use more than one patch in an 8 hour period. Repeat as necessary. Maximum 3 patches per day. Discard patch after single use. Reseal pouch after opening. Children under 12 years of age: ■ Consult a physician.

Other information

Store in a clean, dry place outside of direct sunlight. Protect from excessive moisture

Inactive Ingredients

hydrogenated poly, pentaerythrityl tetra-di-t-butyl hydroxyhydrocinnamate, petroleum, styrene/isoprene copolymer

Questions or comments

Call 1-866-326-1313